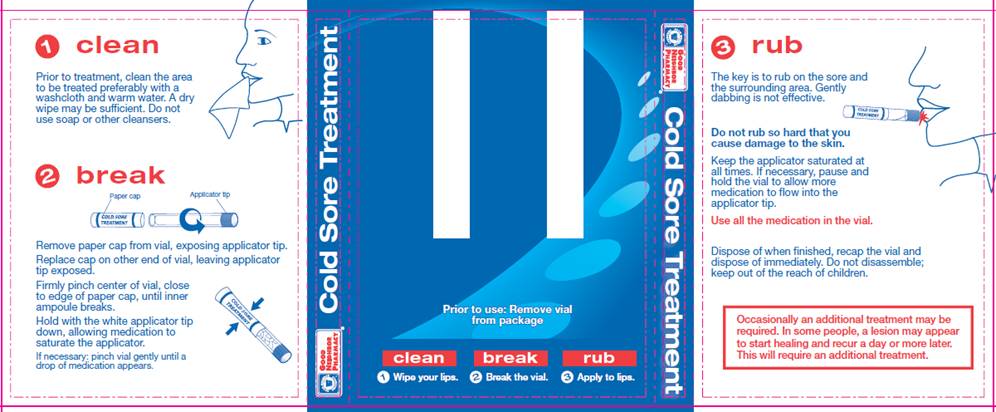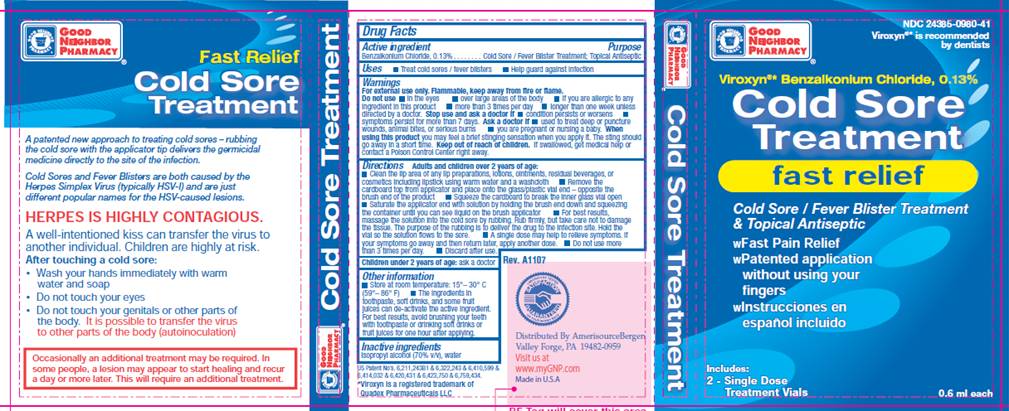 DRUG LABEL: Cold Sore Treatment
NDC: 24385-980 | Form: TINCTURE
Manufacturer: Amerisource Bergen
Category: otc | Type: HUMAN OTC DRUG LABEL
Date: 20100322

ACTIVE INGREDIENTS: Benzalkonium chloride 0.13 mL/1 mL
INACTIVE INGREDIENTS: isopropyl alcohol; water

DRUG FACTS

ACTIVE INGREDIENT

Benzalkonium chloride, 0.13%

PURPOSE

Cold Sore / Fever Blister Treatment; Topical Antiseptic

USES

- Treat cold sores / fever blisters
- Help guard against infection

WARNINGS

For external use only. Flammable, keep away from fire or flame.

Do not use

- in the eyes
- over large areas of the body
- if you are allergic to any ingredient in the product
- more than 3 times per day
- longer than one week unless directed by a doctor.

Stop use and ask a doctor if

- condition persists or worsens
- symptoms persist for more than 7 days

Ask a doctor if

- used to treat deep or puncture wounds, animal bites, or serious burns
- you are pregnant or nursing a baby

When using this product

you may feel a brief stinging sensation when applying it. The sting should go away in a short time.

Keep out of reach of children

If swallowed, get medical help or contact a Poison Control Center right away.

DIRECTIONS

Adults and children over 2 years of age:

- Clean the lip area of any lip preparations, lotions, ointments, residual beverages, or cosmetics including lipstick using warm water and a washcloth
- Remove the cardboard top from applicator and place onto the glass/plastic vial end - opposite the brush end of the product
- Squeeze the cardboard to break the inner glass vial open
- Saturate the applicator end with solution by holding the brush end down and squeezing the container until you can see liquid on the brush applicator
- For best results, massage the solution into the cold sore by rubbing. Rub firmly, but take care not to damage the tissue. The purpose of the rubbing is to deliver the drug to the infection site. Hold the vial so the solution flows to the sore.
- To treat most cold sores, usually one treatment is enough.
- If your symptoms go away and then return later, apply another dose.
- Do not use more than 3 times per day
- Discard after use.

Children under 2 years of age: ask a doctor.

OTHER INFORMATION

- Store at room temperature: 15° - 30° C (59° - 86° F)
- The ingredients in toothpaste, softdrinks, and some fruit juices can de-activate the active ingredient. For best results, avoid brushing your teeth with toothpaste or drinking soft drinks or fruit juices for one hour after applying.

INACTIVE INGREDIENTS

isopropyl alcohol, water

PACKAGE INFORMATION - TRIFOLD INNER

1. CLEAN
Prior to treatment, clean the area to be treated preferably with a washcloth and warm water. A dry wipe may be sufficient. Do not use soap or other cleansers.
2. BREAK
Remove paper cap from vial, exposing applicator tip.
Replace cap on other end of vial, leaving applicator tip exposed.
Firmly pinch center of vial, close to edge of paper cap, until inner ampoule breaks.
Hold with the white applicator tip down, allowing medication to saturate the applicator.
If necessary: pinch vial gently until a drop of medication appears.
Prior to use: Remove vial from package
3. RUB
The key is to rub on the sore and the surrounding area. Gently dabbing is not effective.
Do not rub so hard that you cause damage to the skin.
Keep the applicator saturated at all times. If necessary, pause and hold the vial to allow more medication to flow into the applicator tip.
Use all the medication in the vial.
Dispose of when finished, recap the vial and dispose of immediately. Do not disassemble; keep out of reach of children.
Occasionally an additional treatment may be required. In some people, a lesion may appear to start healing and recur a day or more later. This will require an additional treatment.

PACKAGE INFORMATION - TRIFOLD OUTER

Good Neighbor Pharmacy®
NDC 24385-0980-41
Viroxyn®* is recommended by dentists
Viroxyn®* Benzalkonium Chloride 0.13%
Cold Sore
Treatment
fast relief
Cold Sore / Fever Blister Treatment
and Topical Antiseptic
wFast Pain Relief
wPatented Application without using your fingers
wInstrucciones en espanol incluido
Includes 2 Single Dose Treatment Vials
0.6 mL each
Distributed by Amerisource Bergen
Valley Forge, PA 19482-0959
Visit us at www.myGNP.com
Made in USA
US Patent No’s 6,211,243B1 and 6,322,243 and 6,410,599 and
6,414,032 and 6,420,431 and 6,423,750 and 6,759,434.
*Viroxyn® is a registered trademark of Quadex Pharmaceuticals, LLC
A patented new approach to treating cold sores - rubbing the cold sore with the applicator tip delivers the germicidal medicine directly to the site of the infection.
Cold Sores and Fever Blisters are both caused by the Herpes Simplex virus (typically HSV-1) and are just different popular names for the HSV-caused lesions.
HERPES IS HIGHLY CONTAGIOUS.
A well-intentioned kiss can transfer the virus to another individual. Children are highly at risk.
After touching a cold sore:

- Wash your hands immediately with warm water and soap
- Do not touch your eyes
- Do not touch your genitals or other parts of the body. It is possible to transfer the virus to other parts of the body (autoinoculation)

Occasionally an additional treatment may be required. In some people, a lesion may appear to start healing and recur a day or more later. This will require an additional treatment.